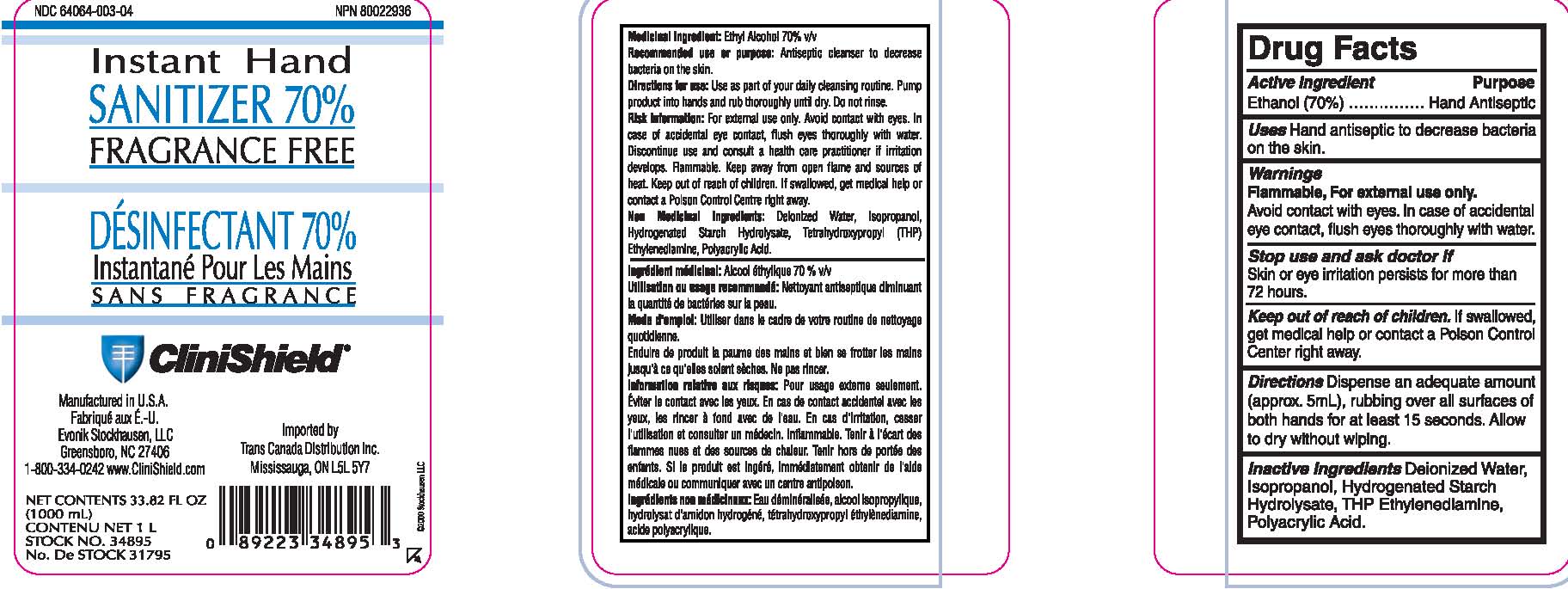 DRUG LABEL: Instant Hand Sanitizer
NDC: 64064-003 | Form: LIQUID
Manufacturer: Evonik Stockhausen, LLC
Category: otc | Type: HUMAN OTC DRUG LABEL
Date: 20110906

ACTIVE INGREDIENTS: ALCOHOL 70 mL/100 mL
INACTIVE INGREDIENTS: WATER; ISOPROPYL ALCOHOL; EDETOL; CARBOMER HOMOPOLYMER TYPE C

Drug Facts

Active Ingredient

Ethanol (70%)

Purpose

Hand Antiseptic

Uses

Hand antiseptic to decrease bacteria on the skin.

Warnings

Flammable, For external use only.

Avoid contact with eyes. In case of accidental eye contact, flush eyes thoroughly with water.

Stop use and ask doctor if

Skin or eye irritation persists for more than 72 hours

KEEP OUT OF REACH OF CHILDREN

If swallowed, get medical help or contact a Poison Control Center right away.

Directions

- Dispense an adequate amount (approx. 5 mL), rubbing all surfaces of both hands for at least15 seconds.
- Allow to dry without wiping.

Inactive Ingredients

Deionized Water, Isopropanol, Hydrogenated Starch Hydrolysate, Carbomer, THP Ethylendiamine, Polyacrylic Acid.

Principal Display Panel

NDC 64064-003-04

Instant Hand

Sanitizer 70%

No Rinsing

Desinfectant

Instantane Pour Les Mains

Sans Rincage

Clinishield

Manufactured in U.S.A.

Fabrique Aux E.-U.

Evonik Stockhausen, LLC

Greensboro, NC 27406

1-800-334-0242 www.CliniShield.com

Imported by

Trans Canada Distribution Inc.

Mississauga, ON L5L 5Y7

Net Contents 33.82 Fl Oz

1000 (mL)

Contenu Net 1 L

Stock No. 31795

No. De Stock 31795